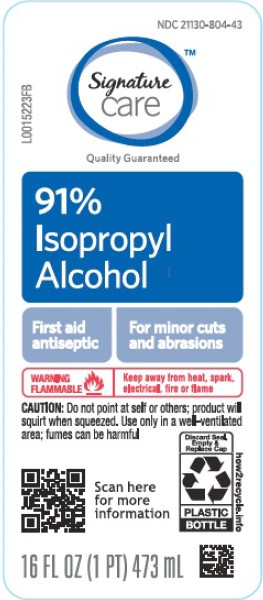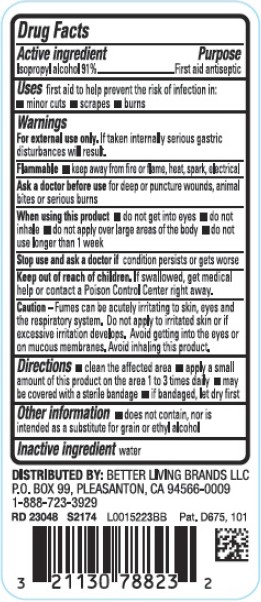 DRUG LABEL: Isopropyl Alcohol
NDC: 21130-804 | Form: LIQUID
Manufacturer: Better Living Brands, LLC
Category: otc | Type: HUMAN OTC DRUG LABEL
Date: 20260224

ACTIVE INGREDIENTS: ISOPROPYL ALCOHOL 91 mL/100 mL
INACTIVE INGREDIENTS: WATER

Signature Care 804.003/804AA
91% Isopropyl Alcohol

Active Ingredient

Isopropyl alcohol 91%

Purpose

First aid antiseptic

Uses

first aid to help prevent the risk of infection in:

- minor cuts
- scrapes
- burns

Warnings

For external use only. If taken internally serious gastric disturbances will result.

Flammable. Keep away from fire or flame, heat, spark, electrical.

Ask a doctor before use

for deep or puncture wounds, animal bites or serious burns

When using this product

- do not get into eyes
- do not inhale
- do not apply over large areas of the body
- do not use longer than 1 week

Stop use and ask a doctor if

condition persists or gets worse

Keep out of reach of children.

If swallowed, get medical help or contact a Poison Control Center right away.

Caution

Fumes can be acutely irritating to skin, eyes and respiratory system. Do not apply to irritated skin or if excessive irritation develops. Avoid getting into the eyes or on mucous membranes. Avoid inhaling this product.

Directions

- clean the affected area
- apply a small amount of this product on the area 1 to 3 times daily
- may be covered with a sterile bandage
- if bandaged, let dry first

Other information

- does not contain, nor is intended as a substitute for grain or ethyl alcohol

Inactive ingredient

water

ADVERSE REACTION

DISTRIBUTED BY BETTER LIVING BRANDS LLC

P.O. BOX 99 PLEASANTON, CA 94566-0009

1-888-723-3929

Pat. D675, 101

principal display panel

NDC 21130-804-43

Signature Care™

Quality Guaranteed

91% Isopropyl Alcohol

First aid antiseptic

For minor cuts and abrasions

WARNING FLAMMABLE - Keep away from heat, spark, electrical, fire or flame

CAUTION: Do not point at self or others; product will squirt when squeezed. Use only in well-ventilated area; fumes can be harmful

Scan for more information

Discard Seal, Empty & Replace Cap

PLASTIC BOTTLE

how2recycle.info

16 FL OZ (1 PT) 473 mL